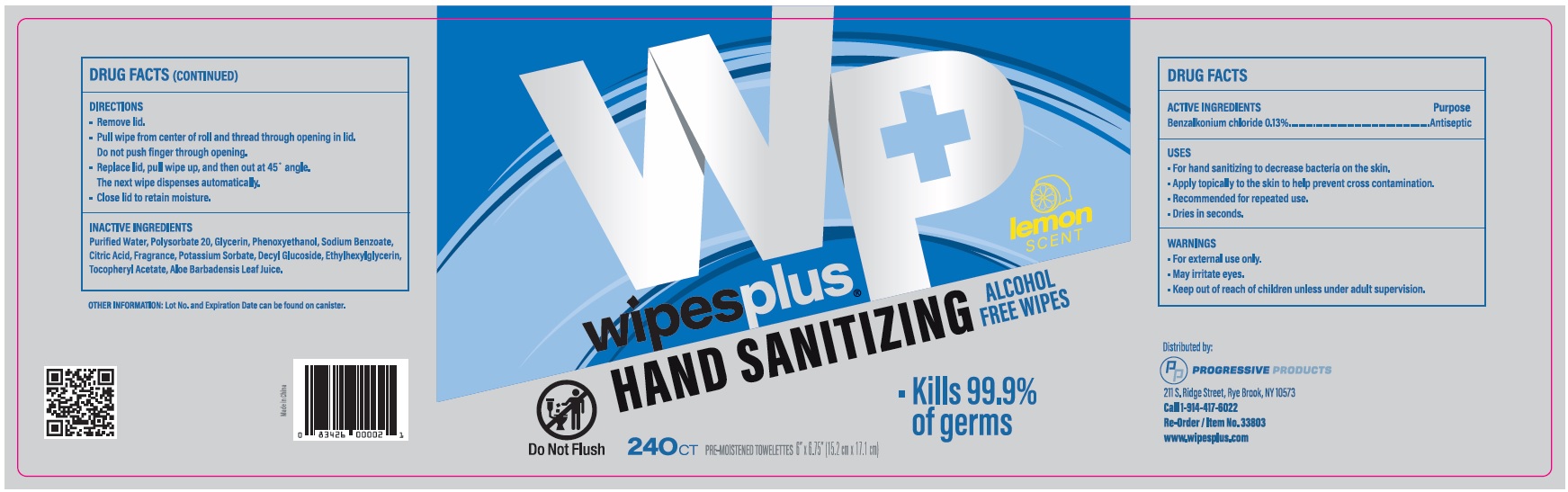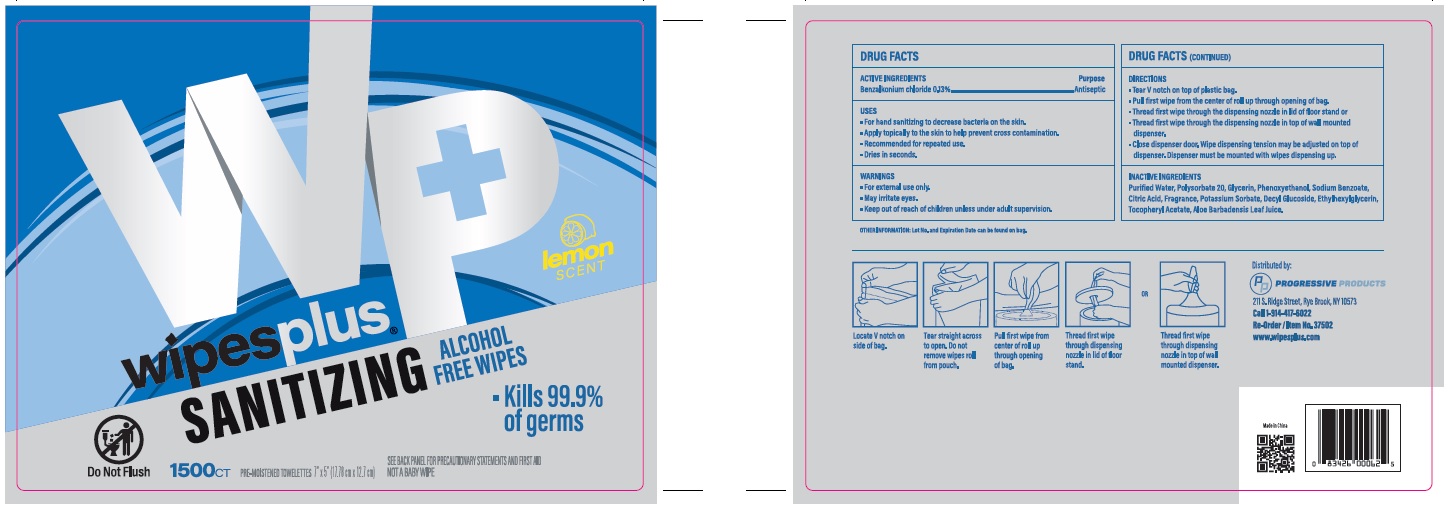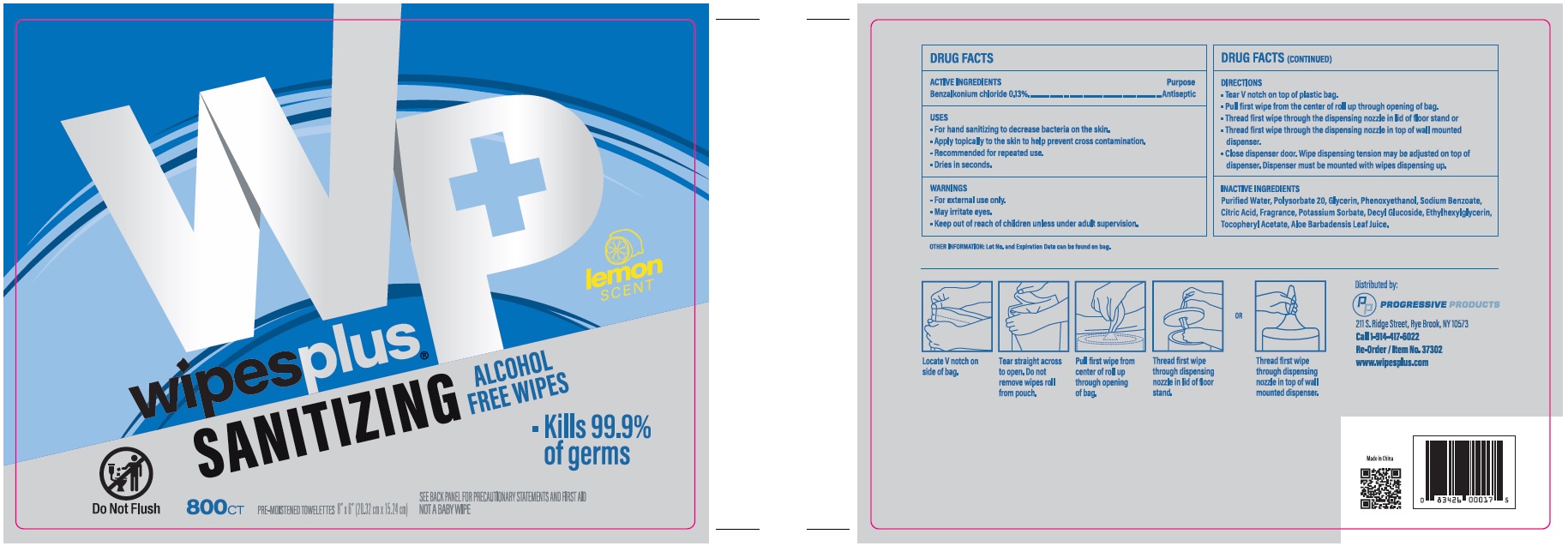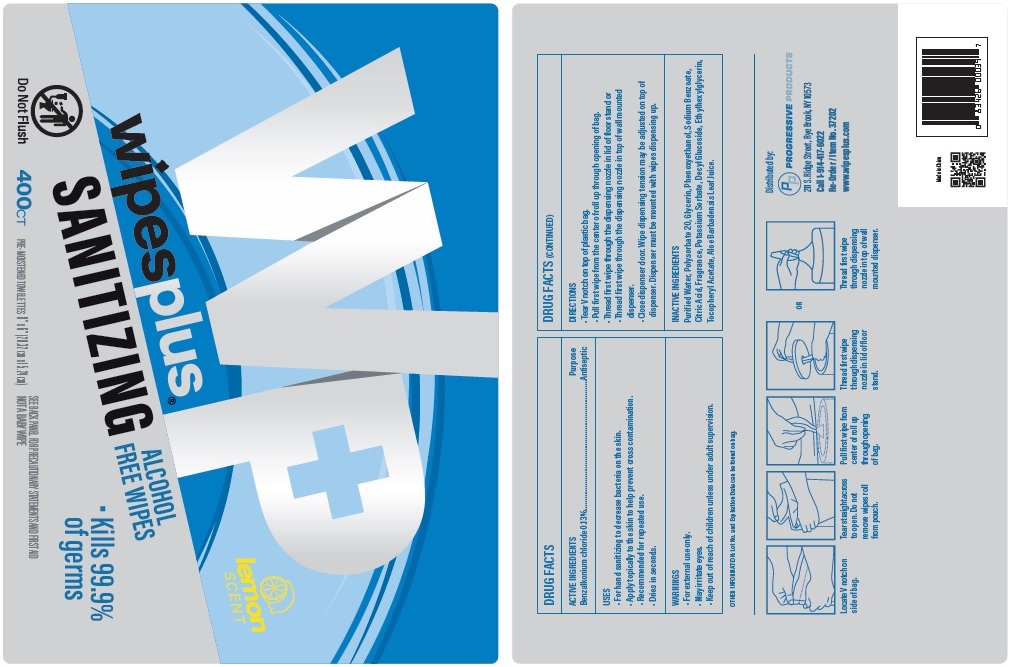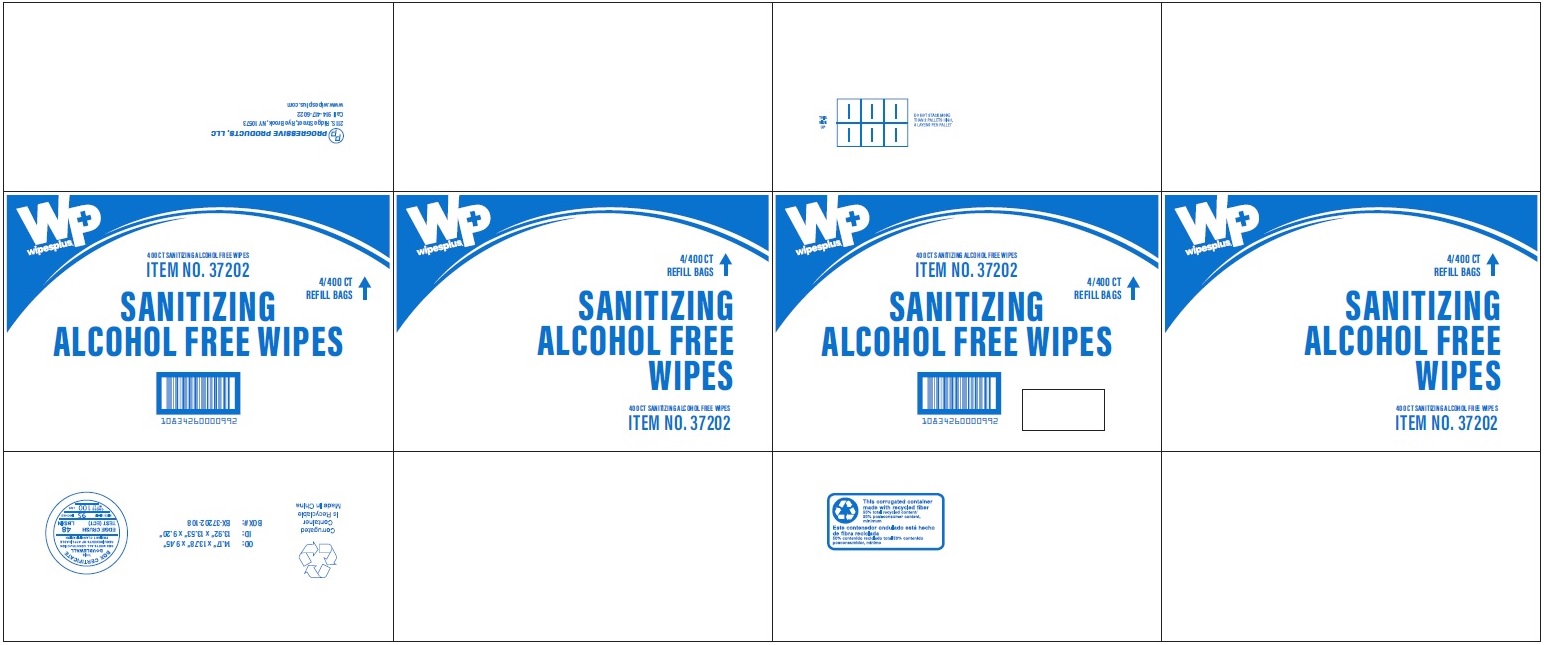 DRUG LABEL: Wipesplus Sanitizing Alcohol Free Wipes
NDC: 67151-343 | Form: CLOTH
Manufacturer: Progressive Products, LLC
Category: otc | Type: HUMAN OTC DRUG LABEL
Date: 20230315

ACTIVE INGREDIENTS: BENZALKONIUM CHLORIDE 0.13 g/100 1
INACTIVE INGREDIENTS: WATER; ALOE VERA LEAF; CITRIC ACID MONOHYDRATE; POTASSIUM SORBATE; POLYSORBATE 20; GLYCERIN; PHENOXYETHANOL; SODIUM BENZOATE; DECYL GLUCOSIDE; ETHYLHEXYLGLYCERIN; .ALPHA.-TOCOPHEROL ACETATE

Drug Facts

Active Ingredients

Benzalkonium Chloride 0.13%

Purpose

Antiseptic

Uses

- For hand sanitizing to decrease bacteria on the skin.
- Apply topically to the skin to help prevent cross contamination.
- Recommended for repeated use.
- Dries in seconds.

Warnings

- For external use only.
- May irritate eyes.

Keep out of the reach of children unless under adult supervision

Directions

- Tear V notch on top of plastic bag.
- Pull first wipe from the center of roll up through opening of bag.
- Thread first wipe through the dispensing nozzle in lid of floor stand or
- Thread first wipe through dispensing nozzle in top of wll mounted dispenser.
- Close dispenser door. Wipe dispensing tension may be adjusted on top of dispenser. Dispenser must be mounted with wipes dispensing up.

Inactive Ingredient

Purified Water, Polysorbate 20, Glycerin, Phenoxyethanol, Sodium Benzoate, Citric Acid, Fragrance, Potassium Sorbate, Decyl Glucoside, Ethylhexylglycerin, Tocopheryl Acetate, Aloe Barbadensis Leaf Juice.

Principal Display Panel

Wipesplus

SANITIZING ALCOHOL FREE WIPES

Kills 99.9% of germs

240CT

1500CT

800CT

400CT